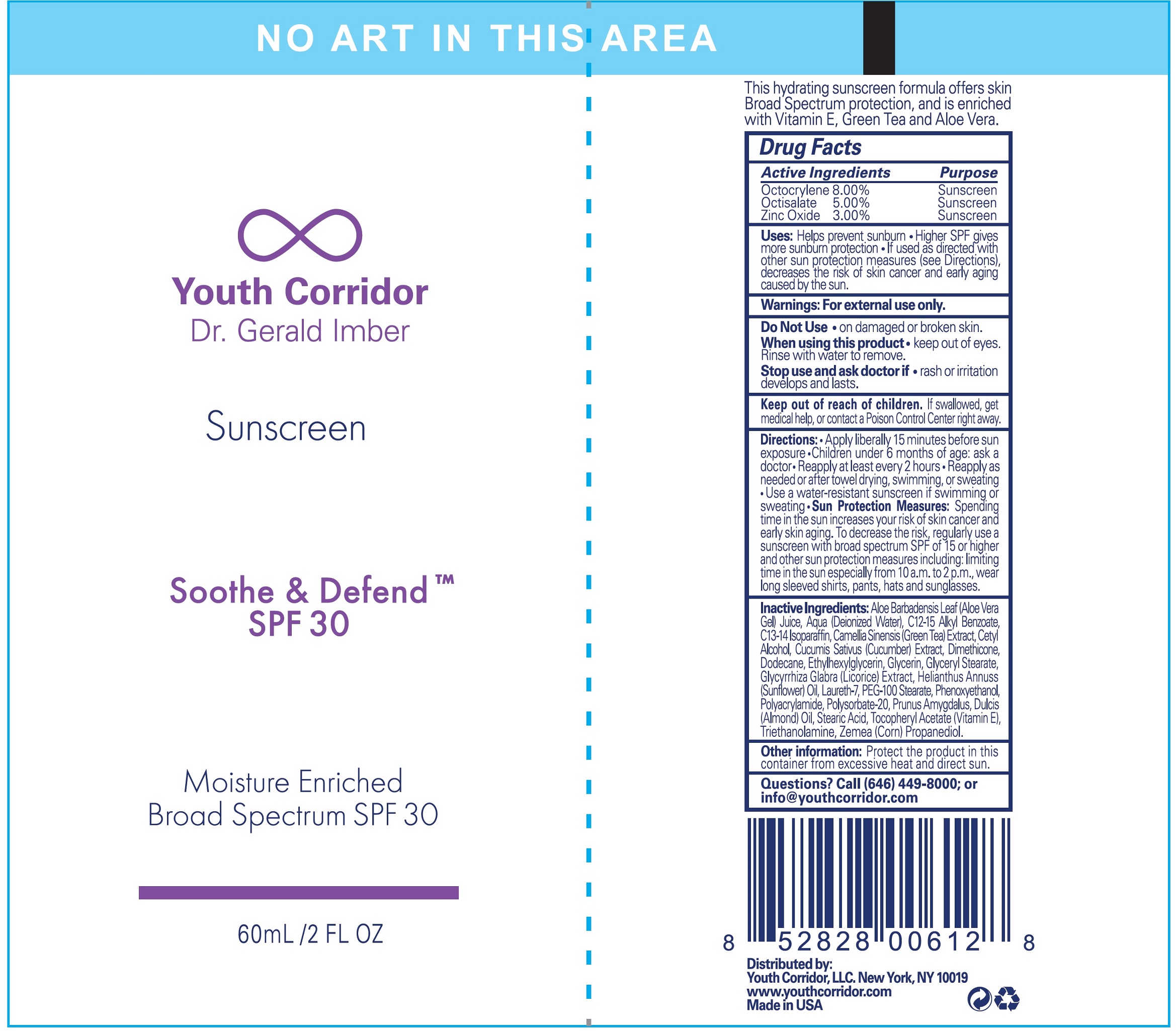 DRUG LABEL: YOUTH CORRIDOR Soothe and Defend SPF-30
NDC: 81201-111 | Form: CREAM
Manufacturer: Youth Corridor
Category: otc | Type: HUMAN OTC DRUG LABEL
Date: 20231111

ACTIVE INGREDIENTS: OCTOCRYLENE 80 mg/1 mL; OCTISALATE 50 mg/1 mL; ZINC OXIDE 30 mg/1 mL
INACTIVE INGREDIENTS: ALOE VERA LEAF; WATER; ALKYL (C12-15) BENZOATE; C13-14 ISOPARAFFIN; GREEN TEA LEAF; CETYL ALCOHOL; CUCUMBER; DIMETHICONE; DODECANE; ETHYLHEXYLGLYCERIN; GLYCERIN; GLYCERYL MONOSTEARATE; LICORICE; HELIANTHUS ANNUUS FLOWERING TOP; LAURETH-7; PEG-100 STEARATE; PHENOXYETHANOL; POLYSORBATE 20; ALMOND; STEARIC ACID; .ALPHA.-TOCOPHEROL ACETATE; TROLAMINE; CORN

YOUTH CORRIDOR Soothe & Defend SPF-30

Active Ingredients

Octocrylene 8.00%

Octisalate 5.00%

Zinc Oxide 3.00%

Purpose

Sunscreen

Uses:

- Helps prevent sunburn.
- Higher SPF gives more sunburn protection
- If used as directed with other sun protection measures (see Directions), decreases the risk of skin cancer and early skin aging caused by the sun.

Warnings:

For externel use only.

Do Not Use

- on damaged or broken skin.

When using this product

- keep out of eyes. Rinse with water to remove.

Stop use and ask a doctor if

- rash or irritation develops and lasts.

Keep out of reach of children.

If swallowed, get medical help or contact a Poison Control Center right away.

Directions:

- Apply liberally 15 minutes before sun exposure.
- Children under 6 months of age:ask a doctor
- Reapply at least every 2 hours.
- Reapply as needed or after towel drying, swimming, or sweating
- Use a water-resistant sunscreen if swimming or sweating.
- Spending time in the sun increases your risk of skin cancer and early skin aging. To decrease this risk, regularly use a sunscreen with a broad spectrum SPF value of 15 or higher and other sun protection measures including: Sun Protection Measures:
- limit time in the sun, especially from 10a.m. - 2.p.m.
- wear long-sleeved shirts, pants, hats, and sunglasses.

Inactive Ingredients:

Aloe Barbadensis Leaf (Aloe Vera Gel) Juice, Aqua (Deionized Water), C12-15 Alkyl Benzoate, C13-14 Isoparaffin, Camellia Sinesis (Green Tea)Extract, Cetyl Alcohol, Cucumis Sativus (Cuumber) Extract, Dimethicone, Dodecane, Ethylhexylglycerin, Glycerin, Glyceryl Stearate, Glycyrrhiza Glabra (Licorice) Extract, Helianthus Annuss(Sunflower)Oil, Laureth-7, PEG-100 Stearate, Phenoxyethanol, Polyacrylamide, Polysorbate-20, Prunus Amygdalus, Dulcis (Almond)Oil, Stearic Acid, Tocopherol Acetate (Vitamin E), Triethanolamine, Zemea (Corn) Propanediol.

Other information:

Protect the product in this container from excessive heat and direct sun.

Questions?

Call (646) 449-8000; or info@youthcorridor.com